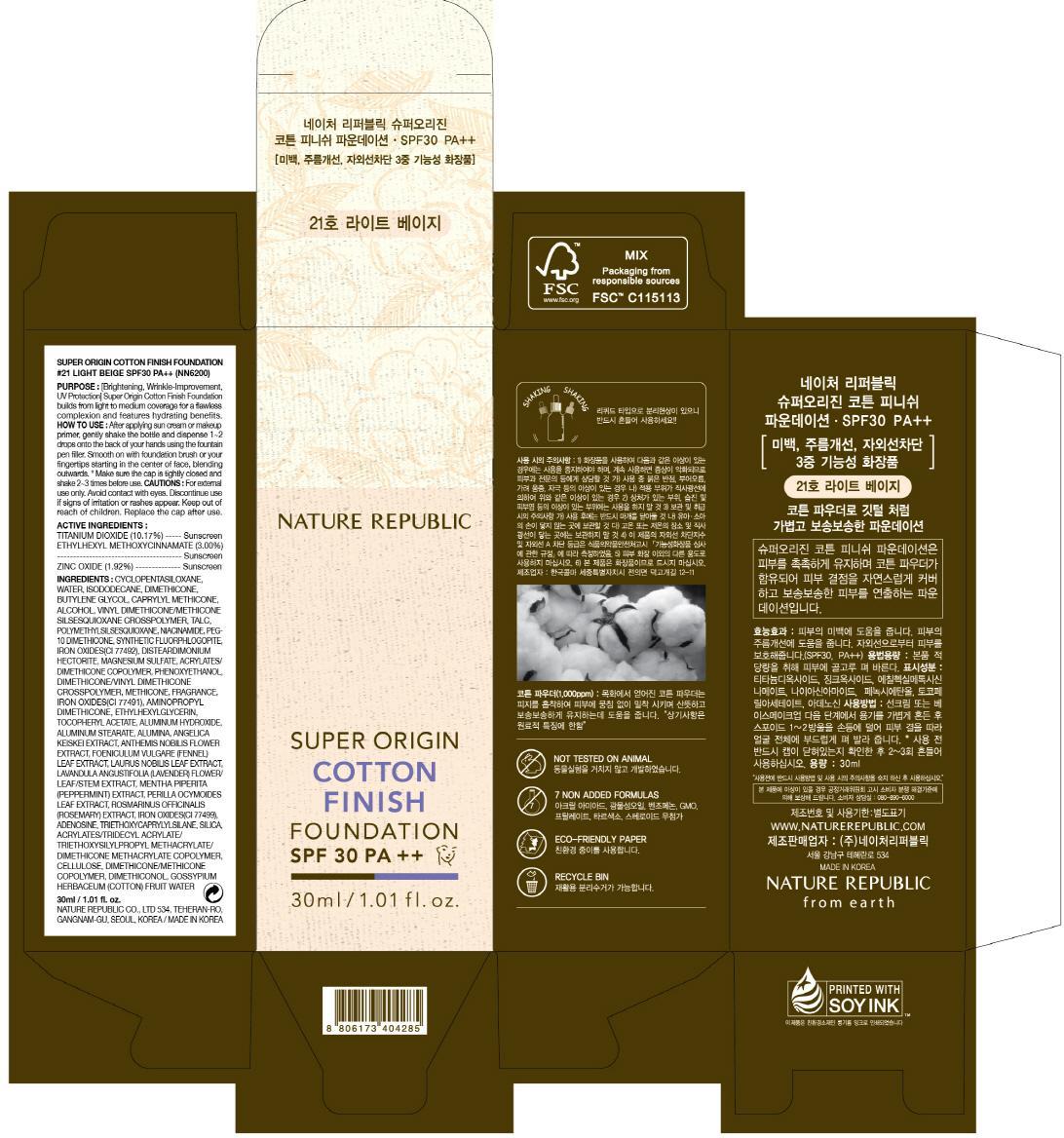 DRUG LABEL: SUPER ORIGIN COTTON FINISH FOUNDATION
NDC: 51346-261 | Form: CREAM
Manufacturer: NATURE REPUBLIC CO., LTD.
Category: otc | Type: HUMAN OTC DRUG LABEL
Date: 20140502

ACTIVE INGREDIENTS: Titanium Dioxide 3.05 mg/30 mL; OCTINOXATE 0.9 mg/30 mL; Zinc Oxide 0.57 mg/30 mL
INACTIVE INGREDIENTS: WATER; DIMETHICONE

ACTIVE INGREDIENT

Active Ingredients: Titanium Dioxide 10.17%, Ethylhexyl Methoxycinnamate 3.00%, Zinc Oxide 1.92%

INACTIVE INGREDIENT

Inactive Ingredients:
CYCLOPENTASILOXANE, WATER, ISODODECANE, DIMETHICONE, BUTYLENE GLYCOL, CAPRYLYL METHICONE, ALCOHOL, VINYL DIMETHICONE/METHICONE SILSESQUIOXANE CROSSPOLYMER, TALC, POLYMETHYLSILSESQUIOXANE, NIACINAMIDE, PEG-10 DIMETHICONE, SYNTHETIC FLUORPHLOGOPITE, IRON OXIDES(CI 77492), DISTEARDIMONIUM HECTORITE, MAGNESIUM SULFATE, ACRYLATES/DIMETHICONE COPOLYMER, PHENOXYETHANOL, DIMETHICONE/VINYL DIMETHICONE CROSSPOLYMER, METHICONE, FRAGRANCE, IRON OXIDES(CI 77491), AMINOPROPYL DIMETHICONE, ETHYLHEXYLGLYCERIN, TOCOPHERYL ACETATE, ALUMINUM HYDROXIDE, ALUMINUM STEARATE, ALUMINA, ANGELICA KEISKEI EXTRACT, ANTHEMIS NOBILIS FLOWER EXTRACT, FOENICULUM VULGARE (FENNEL) LEAF EXTRACT, LAURUS NOBILIS LEAF EXTRACT, LAVANDULA ANGUSTIFOLIA (LAVENDER) FLOWER/LEAF/STEM EXTRACT, MENTHA PIPERITA (PEPPERMINT) EXTRACT,
PERILLA OCYMOIDES LEAF EXTRACT, ROSMARINUS OFFICINALIS (ROSEMARY) EXTRACT, IRON OXIDES(CI 77499), ADENOSINE, TRIETHOXYCAPRYLYLSILANE, SILICA, ACRYLATES/TRIDECYL ACRYLATE/TRIETHOXYSILYLPROPYL METHACRYLATE/DIMETHICONE METHACRYLATE COPOLYMER, CELLULOSE, DIMETHICONE/METHICONE COPOLYMER, DIMETHICONOL, GOSSYPIUM HERBACEUM (COTTON) FRUIT WATER

PURPOSE

Purpose: Brightening, Wrinkle-Improvement, UV Protection

Cautions

For external use only.
Avoid contact with eyes.
Discontinue use if signs of irritation or rashes appear.
Keep out of reach of children.
Replace the cap after use.

KEEP OUT OF REACH OF CHILDREN

How to Use

After applying sun cream or makeup primer, gently shake the bottle and dispense 1-2 drops onto the back of your hands using the fountain pen filler.
Smooth on with foundation brush or your fingertips starting in the center of face, blending outwards.
Make sure the cap is tightly closed and shake 2-3 times before use.

How to Use

After applying sun cream or makeup primer, gently shake the bottle and dispense 1-2 drops onto the back of your hands using the fountain pen filler.
Smooth on with foundation brush or your fingertips starting in the center of face, blending outwards.
Make sure the cap is tightly closed and shake 2-3 times before use.